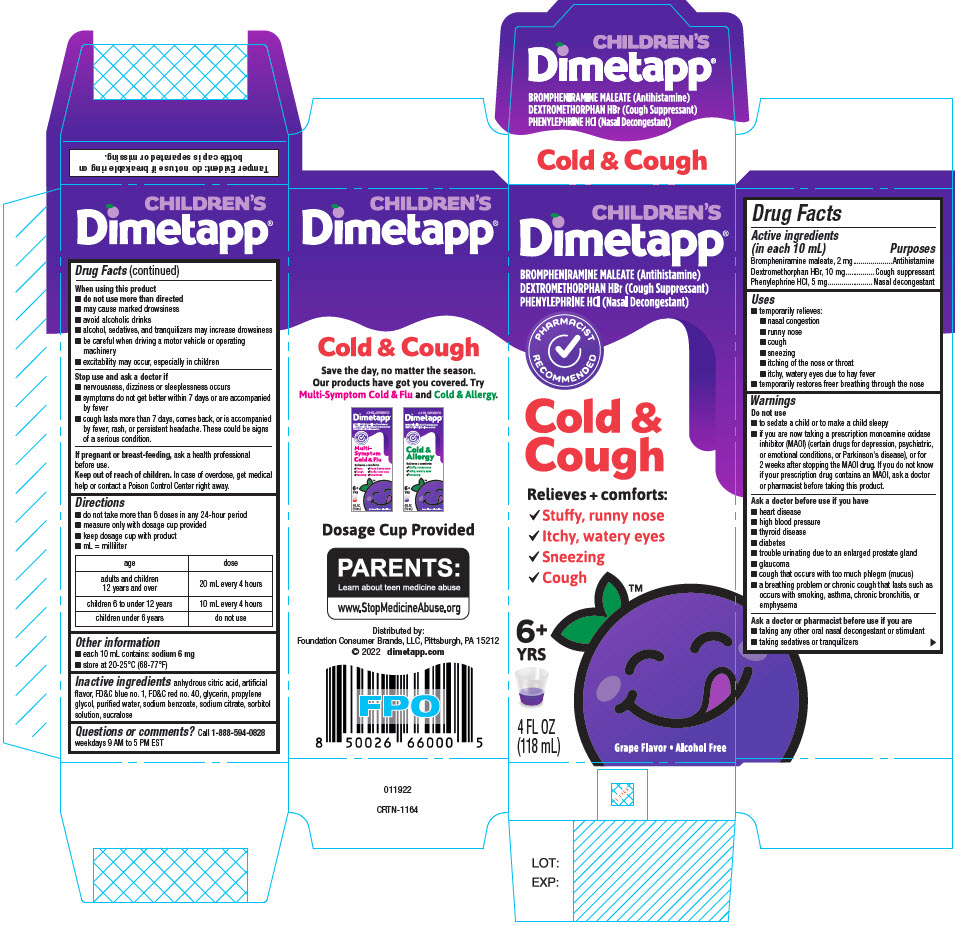 DRUG LABEL: Dimetapp
NDC: 80070-310 | Form: ELIXIR
Manufacturer: Foundation Consumer Brands
Category: otc | Type: HUMAN OTC DRUG LABEL
Date: 20260223

ACTIVE INGREDIENTS: BROMPHENIRAMINE MALEATE 1 mg/5 mL; DEXTROMETHORPHAN HYDROBROMIDE 5 mg/5 mL; PHENYLEPHRINE HYDROCHLORIDE 2.5 mg/5 mL
INACTIVE INGREDIENTS: ANHYDROUS CITRIC ACID; FD&C BLUE NO. 1; FD&C RED NO. 40; GLYCERIN; PROPYLENE GLYCOL; WATER; SODIUM BENZOATE; SODIUM CITRATE, UNSPECIFIED FORM; SORBITOL; SUCRALOSE

Dimetapp®
Cold and Cough

Drug Facts

ACTIVE INGREDIENT

PURPOSE

Active ingredients (in each 10 mL) | Purposes
Brompheniramine maleate, 2 mg | Antihistamine
Dextromethorphan HBr, 10 mg | Cough suppressant
Phenylephrine HCl, 5 mg | Nasal decongestant

Uses

- temporarily relieves:
  - nasal congestion
  - runny nose
  - cough
  - sneezing
  - itching of the nose or throat
  - itchy, watery eyes due to hay fever
- temporarily restores freer breathing through the nose

Warnings

Do not use

- to sedate a child or to make a child sleepy
- if you are now taking a prescription monoamine oxidase inhibitor (MAOI) (certain drugs for depression, psychiatric, or emotional conditions, or Parkinson's disease), or for 2 weeks after stopping the MAOI drug. If you do not know if your prescription drug contains an MAOI, ask a doctor or pharmacist before taking this product.

Ask a doctor before use if you have

- heart disease
- high blood pressure
- thyroid disease
- diabetes
- trouble urinating due to an enlarged prostate gland
- glaucoma
- cough that occurs with too much phlegm (mucus)
- a breathing problem or chronic cough that lasts such as occurs with smoking, asthma, chronic bronchitis, or emphysema

Ask a doctor or pharmacist before use if you are

- taking any other oral nasal decongestant or stimulant
- taking sedatives or tranquilizers

When using this product

- do not use more than directed
- may cause marked drowsiness
- avoid alcoholic beverages
- alcohol, sedatives, and tranquilizers may increase drowsiness
- be careful when driving a motor vehicle or operating machinery
- excitability may occur, especially in children

Stop use and ask a doctor if

- nervousness, dizziness or sleeplessness occurs
- symptoms do not get better within 7 days or are accompanied by fever
- cough lasts more than 7 days, comes back, or is accompanied by fever, rash, or persistent headache. These could be signs of a serious condition.

PREGNANCY OR BREAST FEEDING

If pregnant or breast-feeding,ask a health professional before use.

Keep out of reach of children.In case of overdose, get medical help or contact a Poison Control Center right away.

Directions

- do not take more than 6 doses in any 24-hour period
- measure only with dosage cup provided
- keep dosage cup with product
- mL = milliliter

age | dose
adults and children 12 years and over | 20 mL every 4 hours
children 6 to under 12 years | 10 mL every 4 hours
children under 6 years | do not use

Other information

- each 10 mL contains: sodium 6 mg
- store at 20-25°C (68-77°F)

Inactive ingredients

anhydrous citric acid, artificial flavor, FD&C blue no. 1, FD&C red no. 40, glycerin, propylene glycol, purified water, sodium benzoate, sodium citrate, sorbitol solution, sucralose

Questions or comments?

Call 1-888-594-0828weekdays 9 AM to 5 PM EST

Distributed by:
Foundation Consumer Brands, LLC
Pittsburgh, PA 15212

PRINCIPAL DISPLAY PANEL - 118 mL Bottle Carton

CHILDREN'S
Dimetapp®

BROMPHENIRAMINE MALEATE (Antihistamine)
DEXTROMETHORPHAN HBr (Cough Suppressant)
PHENYLEPHRINE HCl (Nasal Decongestant)

PHARMACIST
RECOMMENDED

Cold &
Cough

Relieves + comforts:

- Stuffy, runny nose
- Itchy, watery eyes
- Sneezing
- Cough

6+
YRS

4 FL OZ
(118 mL)

Grape Flavor • Alcohol Free